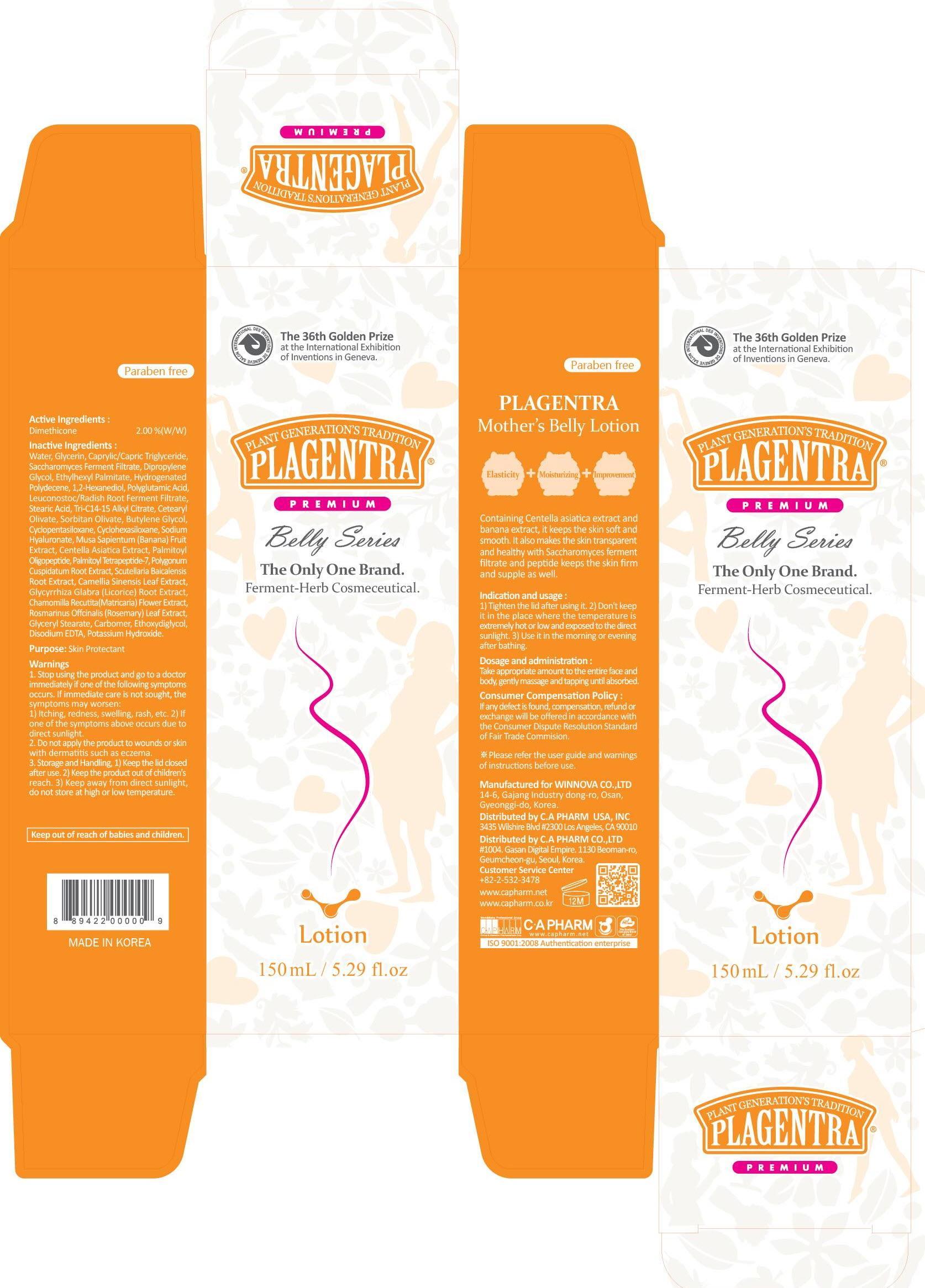 DRUG LABEL: PLAGENTRA MOTHERS BELLY
NDC: 68988-010 | Form: LOTION
Manufacturer: C.A Pharm Co., Ltd.
Category: otc | Type: HUMAN OTC DRUG LABEL
Date: 20141205

ACTIVE INGREDIENTS: Dimethicone 3 mg/150 mL
INACTIVE INGREDIENTS: Water; Glycerin

ACTIVE INGREDIENT

Active Ingredient: Dimethicone 2%

INACTIVE INGREDIENT

Inactive Ingredients:
Water, Glycerin, Caprylic/Capric Triglyceride, Saccharomyces Ferment Filtrate, Dipropylene Glycol, Ethylhexyl Palmitate, Hydrogenated Polydecene, 1,2-Hexanediol, Polyglutamic Acid, Leuconostoc/Radish Root Ferment Filtrate, Stearic Acid, Tri-C14-15 Alkyl Citrate, Cetearyl Olivate, Sorbitan Olivate, Butylene Glycol, Cyclopentasiloxane, Cyclohexasiloxane, Sodium Hyaluronate, Musa Sapientum (Banana) Fruit Extract, Centella Asiatica Extract, Palmitoyl Oligopeptide, Palmitoyl Tetrapeptide-7, Polygonum Cuspidatum Root Extract, Scutellaria Baicalensis Root Extract, Camellia Sinensis Leaf Extract, Glycyrrhiza Glabra (Licorice) Root Extract, Chamomilla Recutita(Matricaria) Flower Extract, Rosmarinus Offcinalis (Rosemary) Leaf Extract, Glyceryl Stearate, Carbomer, Ethoxydiglycol, Disodium EDTA, Potassium Hydroxide

PURPOSE

Purpose: Skin Protectant

WARNINGS

1. Stop using the product and go to a doctor immediately if one of the following symptoms occurs. If immediate care is not sought, the symptoms may worsen:
1) Itching, redness, swelling, rash, etc. 2) If one of the symptoms above occurs due to direct sunlight.
2. Do not apply the product to wounds or skin with dermatitis such as eczema.
3. Storage and Handling, 1) Keep the lid closed after use. 2) Keep the product out of children's reach. 3) Keep away from direct sunlight, do not store at high or low temperature.

KEEP OUT OF REACH OF CHILDREN

Keep out of reach of babies and children.

INDICATIONS & USAGE

Indication and usage:
1) Tighten the lid after using it. 2) Don't keep it in the place where the temperature is extremely hot or low and exposed to the direct sunlight. 3) Use it in the morning or evening after shower.

DOSAGE & ADMINISTRATION

Dosage and administration:
Take appropriate amount to the entire face and body, gently massage and tapping until absorbed.